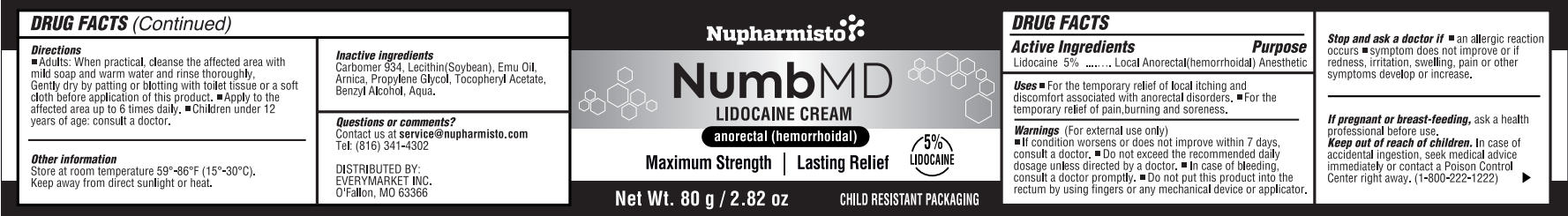 DRUG LABEL: Nupharmisto NumbMD LIDOCAINE cream anorectal (hemorrhoidal)
NDC: 85833-002 | Form: CREAM
Manufacturer: EveryMarket Inc
Category: otc | Type: HUMAN OTC DRUG LABEL
Date: 20260112

ACTIVE INGREDIENTS: LIDOCAINE 4 g/80 g
INACTIVE INGREDIENTS: LECITHIN, SOYBEAN; ARNICA MONTANA; .ALPHA.-TOCOPHEROL ACETATE; AQUA; PROPYLENE GLYCOL; EMU OIL; CARBOMER 934; BENZYL ALCOHOL

Initial Drug Listing - Nupharmisto NumbMD LIDOCAINE CREAM anorectal (hemorrhoidal)

ACTIVE INGREDIENT

Lidocaine 5%

PURPOSE

Local Anorectal(hemorrhoidal) Anesthetic

DOSAGE AND ADMINISTRATION

For the temporary relief of local itching and discomfort associated with anorectal disorders. For the temporary relief of pain,burning and soreness.

WARNINGS

For external use only

- If condition worsens or does not improve within 7 days,consult a doctor.
- Do not exceed the recommended daily dosage unless directed by a doctor.
- In case of bleeding,consult a doctor promptly.
- Do not put this product into the rectum by using fingers or any mechanical device or applicator.

ASK DOCTOR

- an allergic reaction occurs
- symptom does not improve or ifredness, irritation, swelling, pain or othe rsymptoms develop or increase.

PREGNANCY OR BREAST FEEDING

Ask a health professional before use.

KEEP OUT OF REACH OF CHILDREN

In case of accidental ingestion, seek medical advice immediately or contact a Poison Control Center right away.(1-800-222-1222)

INDICATIONS AND USAGE

- Adults: When practical, cleanse the affected area with mild soap and warm water and rinse thoroughly, gently dry by patting or blotting with toilet tissue or a sof tcloth before application of this product.
- Apply to the affected area up to 6 times daily.
- Children under 12years of age: consult a doctor.

OTHER SAFETY INFORMATION

Store at room temperature 59-86F(15-30C). Keep away from direct sunlight or heat.

INACTIVE INGREDIENT

Carbomer 934, Lecithin(Soybean), Emu Oil,Arnica, Propylene Glycol, Tocopheryl Acetate,Benzyl Alcohol, Aqua.

QUESTIONS

- Contact us at service@nupharmisto.com
- Tel:(816)341-4302